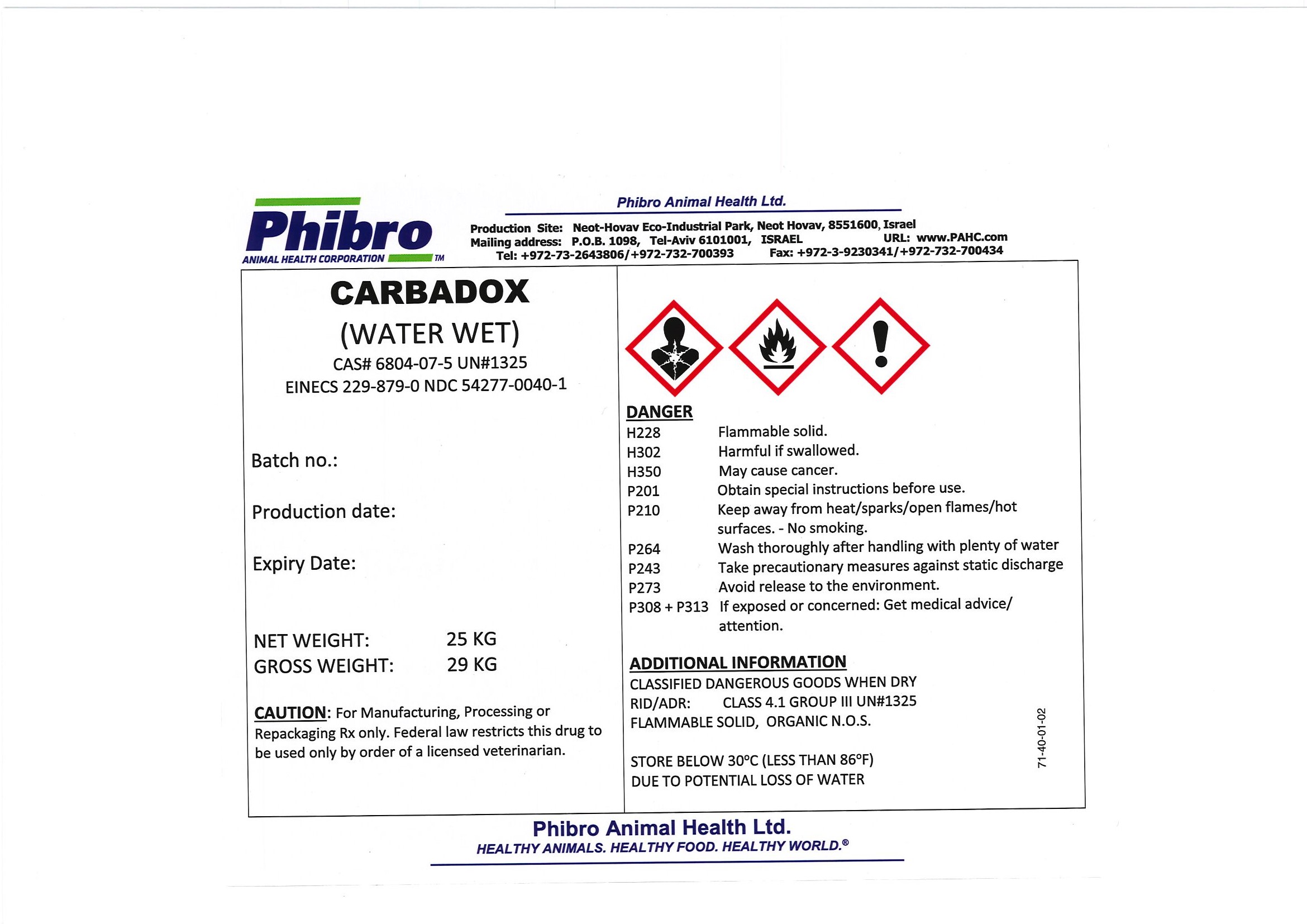 DRUG LABEL: Carbadox
NDC: 54277-0040 | Form: POWDER
Manufacturer: Phibro Animal Health Ltd
Category: other | Type: BULK INGREDIENT - ANIMAL DRUG
Date: 20220525

ACTIVE INGREDIENTS: CARBADOX 1 kg/1 kg

CARBADOX

Carbadox

Add image transcription here...